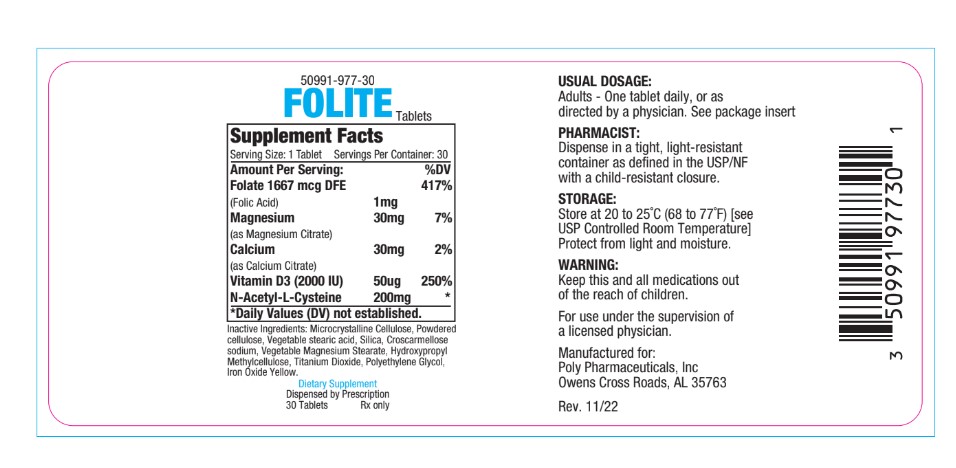 DRUG LABEL: Folite
NDC: 50991-977 | Form: TABLET
Manufacturer: Poly Pharmaceuticals, Inc.
Category: other | Type: DIETARY SUPPLEMENT
Date: 20190805

ACTIVE INGREDIENTS: FOLIC ACID 1 mg/1 1
INACTIVE INGREDIENTS: ACETYLCYSTEINE 200 mg/1 1; CHOLECALCIFEROL 50 [iU]/1 1; CALCIUM CITRATE 30 mg/1 1; MAGNESIUM CITRATE 30 mg/1 1

Folite Tablet

Description

Folite Tablets is a dietary supplement intended for oral administration

Indication and Usage

Folite is indicated for folic acid supplementation and general nutritional support. May also be recommended for patients who are of advancing
age or suffer from improper food intake.

Precaution

Folic Acid in doses above 0.1 mg daily may obscure pernicious anemia in that hematologic remission can occur while neurological manifestations remain progressive.

Warnings

KEEP THIS AN ALL MEDICATION OUT OF REACH OF CHILDREN.

For use under the supervision of a licensed physician. Dispense in a tight, light resistant container as defined in the USP/NF with a child-resistant closure.

Storage

Store at 20 to 25°C (68 to 77°F) [see USP Controlled Room Temperature|
Protect from light and moisture.

Dosage and Administration

Adults-one tablet daily or as directed by physician.

Safety and effectiveness in pediatric patients have not been established.

Dispense in a tight, light-resistant container as defined in the USP/NF with a child-resistant closure.